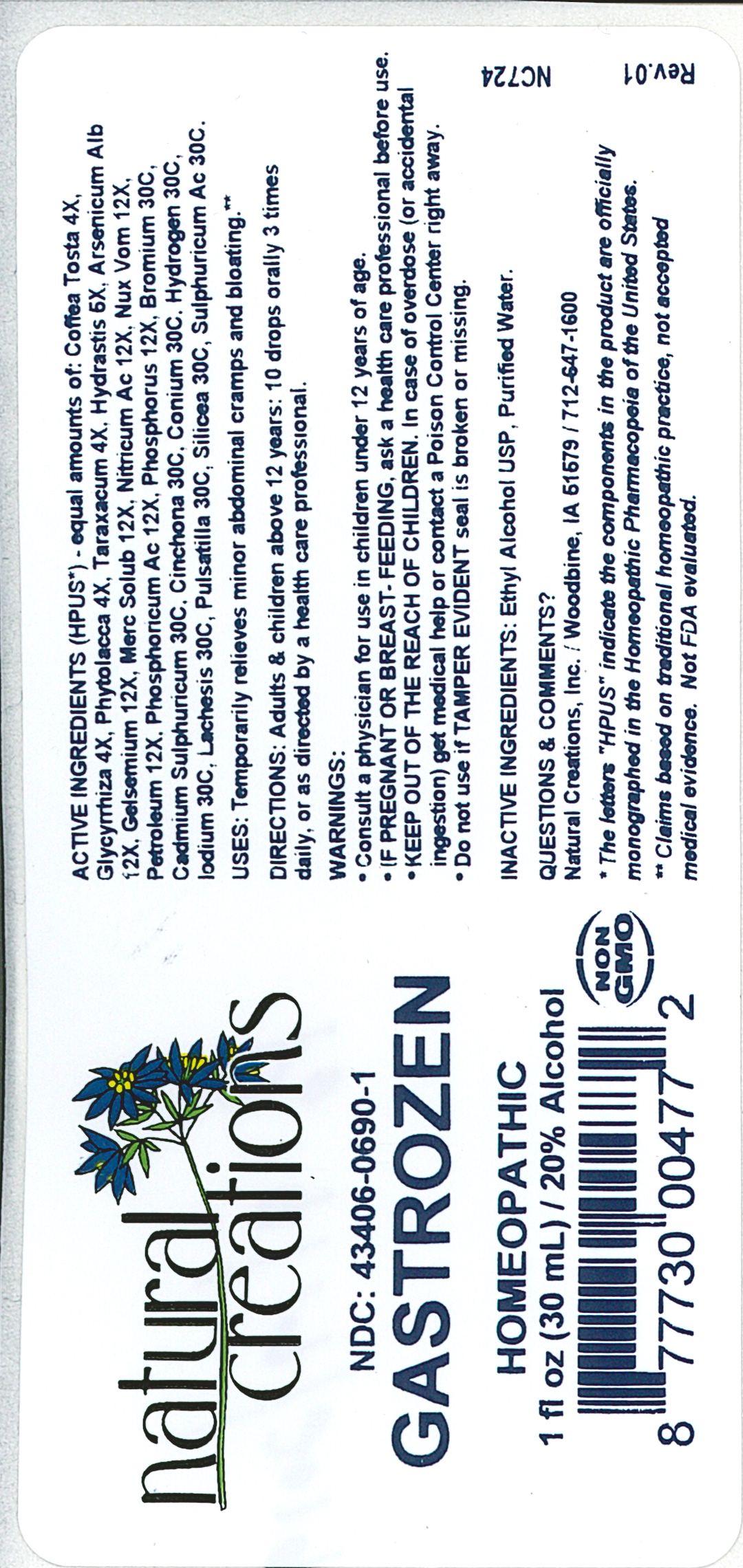 DRUG LABEL: Gastrozen
NDC: 43406-0690 | Form: LIQUID
Manufacturer: Natural Creations, Inc
Category: homeopathic | Type: HUMAN OTC DRUG LABEL
Date: 20181221

ACTIVE INGREDIENTS: COFFEA ARABICA SEED, ROASTED 4 [hp_X]/1 mL; GLYCYRRHIZA GLABRA 4 [hp_X]/1 mL; PHYTOLACCA AMERICANA ROOT 4 [hp_X]/1 mL; TARAXACUM OFFICINALE 4 [hp_X]/1 mL; GOLDENSEAL 6 [hp_X]/1 mL; ARSENIC TRIOXIDE 12 [hp_X]/1 mL; GELSEMIUM SEMPERVIRENS ROOT 12 [hp_X]/1 mL; MERCURIUS SOLUBILIS 12 [hp_X]/1 mL; NITRIC ACID 12 [hp_X]/1 mL; STRYCHNOS NUX-VOMICA SEED 12 [hp_X]/1 mL; KEROSENE 12 [hp_X]/1 mL; PHOSPHORIC ACID 12 [hp_X]/1 mL; PHOSPHORUS 12 [hp_X]/1 mL; BROMINE 30 [hp_C]/1 mL; CADMIUM SULFATE 30 [hp_C]/1 mL; CINCHONA OFFICINALIS BARK 30 [hp_C]/1 mL; CONIUM MACULATUM FLOWERING TOP 30 [hp_C]/1 mL; HYDROGEN 30 [hp_C]/1 mL; IODINE 30 [hp_C]/1 mL; LACHESIS MUTA VENOM 30 [hp_C]/1 mL; PULSATILLA VULGARIS WHOLE 30 [hp_C]/1 mL; SILICON DIOXIDE 30 [hp_C]/1 mL; SULFURIC ACID 30 [hp_C]/1 mL
INACTIVE INGREDIENTS: ALCOHOL; WATER

Gastrozen

ACTIVE INGREDIENT

ACTIVE INGREDIENTS (*HPUS) - equal amounts of: Coffea Tosta 4X, Glycyrrhiza 4X, Phytolacca 4X, Taraxacum 4X, Hydrastis 6X, Arsenicum Alb 12X, Gelsemium 12X, Merc Solub 12X, Nitricum Ac 12X, Nux Vom 12X, Petroleum 12X, Phosphoricum Ac 12X, Phosphorus 12X, Bromium 30C, Cadmium Sulphuricum 30C, Cinchona 30C, Conium 30C, Hydrogen 30C, Iodium 30C, Lachesis 30C, Pulsatilla 30C, Silicea 30C, Sulphuricum Ac 30C

INDICATIONS AND USAGE

USES: Temporarily relieves minor abdominal cramps and bloating.**

PURPOSE

USES: Temporarily relieves minor abdominal cramps and bloating.**

DOSAGE AND ADMINISTRATION

DIRECTIONS: Adults & children above 12 years: 10 drops orally 3 times daily, or as directed by a health care professional.

KEEP OUT OF REACH OF CHILDREN

KEEP OUT OF THE REACH OF CHILDREN. In case of overdose (or accidental ingestion) get medical help or contact a Poison Control Center right away.

WARNINGS:

- Consult a physician for use in children under 12 years of age.
- IF PREGNANT OR BREAST-FEEDING, ask a health care professional before use.
- KEEP OUT OF THE REACH OF CHILDREN. In case of overdose (or accidental ingestion) get medical help or contact a Poison Control Center right away.
- Do not use if TAMPER EVIDENT seal is broken or missing.

INACTIVE INGREDIENTS: Ethyl Alcohol USP, Purified Water

QUESTIONS & COMMENTS?

Natural Creations, Inc. / Woodbine, IA 51579 / 712-647-1600

REFERENCES

*The letters "HPUS" indicate the components in the product are officially monographed in the Homeopathic Pharmacopeia of the United States.

**Claims based on traditional homeopathic practice, not accepted medical evidence. Not FDA evaluated.

PACKAGE LABEL

NDC:43406-0690-1

Gastrozen

HOMEOPATHIC

1 fl oz (30mL) / 20% Alcohol